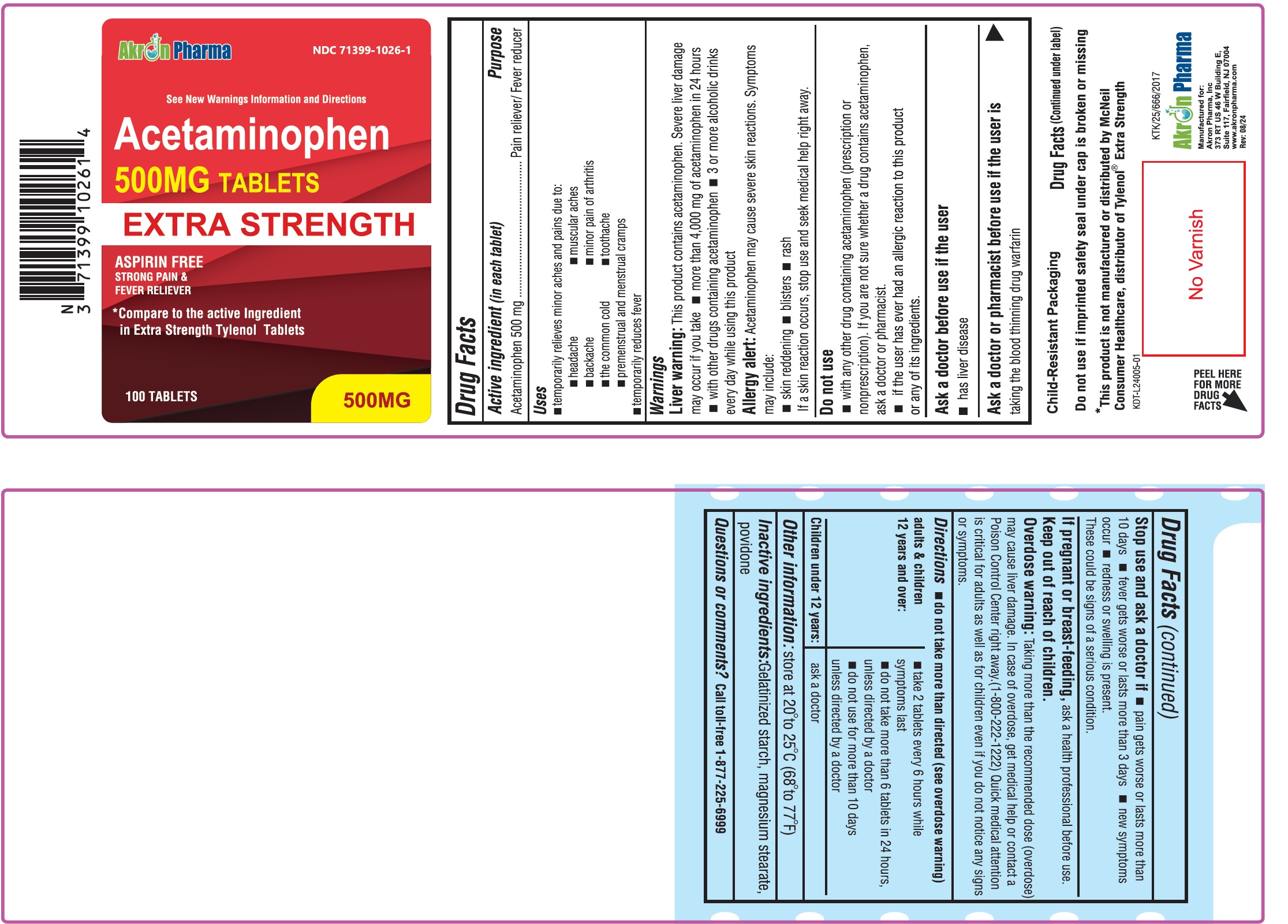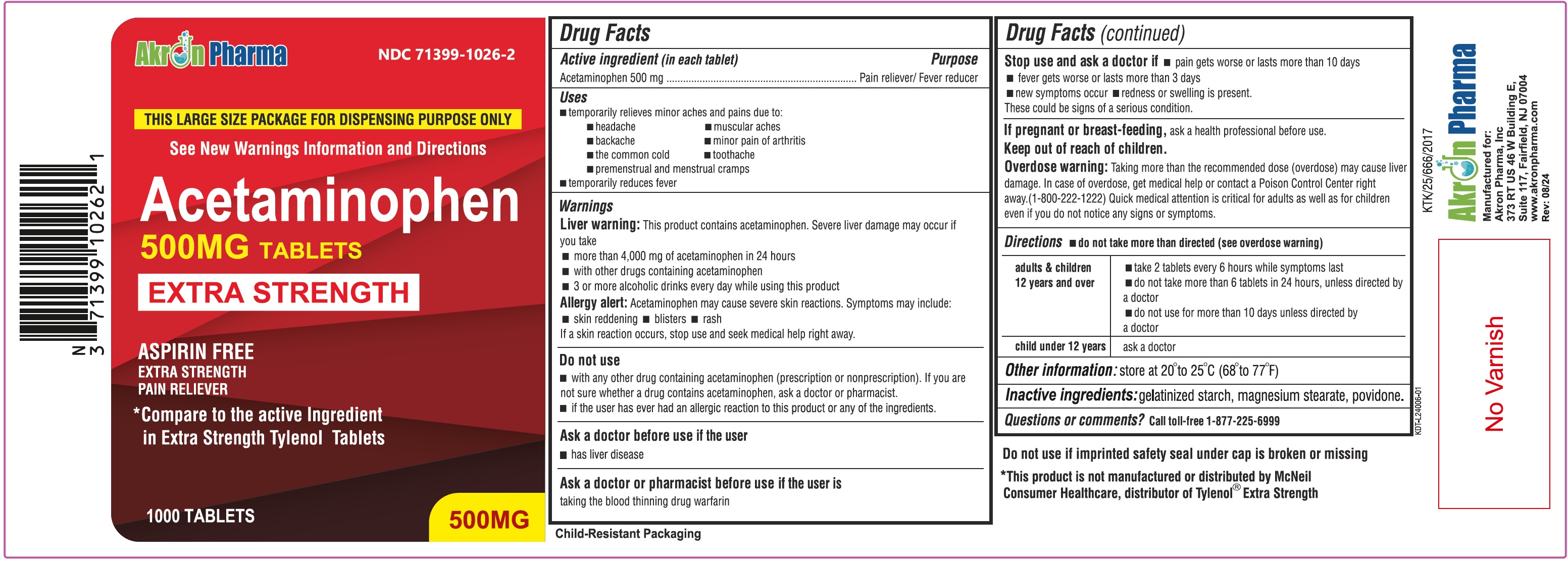 DRUG LABEL: ACETAMINOPHEN
NDC: 71399-1026 | Form: TABLET
Manufacturer: Akron Pharma Inc.
Category: otc | Type: HUMAN OTC DRUG LABEL
Date: 20260119

ACTIVE INGREDIENTS: ACETAMINOPHEN 500 mg/1 1
INACTIVE INGREDIENTS: STARCH, CORN; MAGNESIUM STEARATE; POVIDONE

Acetaminophen 500 mg Tablets
Extra Strength

Active ingredient (in each tablet)

Acetaminophen 500 mg

Purpose

Pain Reliever/Fever Reducer

Uses

To reduce fever and for the temporary relief of minor aches and pains due to:

•headache

•muscular aches

•backache

•minor pain of arthritis

•the common cold

•toothache

•premenstrual and menstrual cramps.

•Temporarily reduces fever.

Warnings

Liver warning:

This product contains acetaminophen. Severe liver damage may occur if

- adult takes more than 4,000 mg of acetaminophen in 24 hours
- child takes more than 5 doses in 24 hours
- taken with other drugs containing acetaminophen
- adult has 3 or more alcoholic drinks every day while using this product

Allergy alert:Acetaminophen may cause severe skin reactions. Symptoms may include:

- skin reddening
- blisters
- rash

If a skin reaction occurs, stop use and seek medical help right away.

Do not use

- with any other drug containing acetaminophen (prescription or non-prescription). If you are not sure whether a drug contains acetaminophen, ask a doctor or pharmacist.
- if the user has ever had an allergic reaction to this product or any of its ingredients.

Ask a doctor before use if the user has

- has liver disease
- is a child with pain of arthritis

Ask a doctor or pharmacist before use if your child istaking the blood thinning drug warfarin

Stop use and ask a doctor if:

- pain gets worse or lasts more than 10 days (for adults) or 5 days (for children)
- fever gets worse or lasts more than 3 days
- new symptoms occur
- redness or swelling is present.

These could be signs of a serious condition.

PREGNANCY OR BREAST FEEDING

If pregnant or breast-feeding,ask a health professional before use.

Keep out of reach of children.

Overdose Warning:

Taking more than the recommended dose (overdose) may cause liver damage. In case of overdose, get medical help or contact a Poison Control Center right away.(1-800-222-1222)

Quick medical attention is critical for adults as well as for children even if you do not notice any signs or symptoms.

Directions - do not take more than directed (see overdose warning)

adults & children 12 years and over | - take 2 tablets every 6 hours while symptoms last - do not take more than 6 tablets in 24 hours, unless directed by a doctor - do not use for more than 10 days unless directed by a doctor
children under 12 years | - ask a doctor

Other information

- store at 20° to 25°C (68° to 77°F)

Inactive Ingredients:

Gelatinized starch, magnesium stearate, povidone

Questions or Comments?

Call toll-free 1-877-225-6999

Manufactured for
Akron Pharma, Inc.,

373 RT US46 W Building E,

Suite 117, Fairfeld, NJ - 07004

*This product is not manufactured or distributed by Johnson and Johnson, consumer inc., distributor of regular Tylenol Tablets.